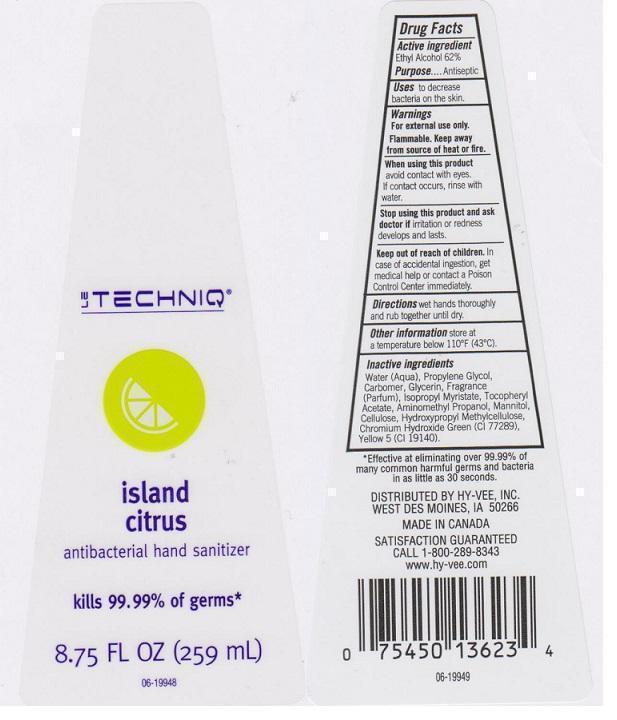 DRUG LABEL: LE TECHNIQ
NDC: 42507-058 | Form: LIQUID
Manufacturer: HYVEE INC
Category: otc | Type: HUMAN OTC DRUG LABEL
Date: 20141124

ACTIVE INGREDIENTS: ALCOHOL 620 mg/1 mL
INACTIVE INGREDIENTS: WATER; PROPYLENE GLYCOL; CARBOMER 934; GLYCERIN; ISOPROPYL MYRISTATE; .ALPHA.-TOCOPHEROL ACETATE; AMINOMETHYLPROPANOL; MANNITOL; POWDERED CELLULOSE; HYPROMELLOSES; CHROMIUM HYDROXIDE GREEN; FD&C YELLOW NO. 5

DRUG FACTS

ACTIVE INGREDIENT

ETHYL ALCOHOL 62%

PURPOSE

ANTISEPTIC

USES

TO DECREASE BACTERIA ON THE SKIN

WARNINGS

FOR EXTERNAL USE ONLY. FLAMMABLE. KEEP AWAY FROM SOURCE OF HEAT OR FIRE

WHEN USING THIS PRODUCT

AVOID CONACT WITH EYES. IF CONTACT OCCURS, RINSE WITH WATER

STOP USING THIS PRODUCT AND ASK DOCTOR IF

IRRITATION OR REDNESS DEVELOPS AND LASTS

KEEP OUT OF REACH OF CHILDREN

IN CASE OF ACCIDENTAL INGESTION, GET MEDICAL HELP OR CONTACT A POISON CONTROL CENTER IMMEDIATELY

DIRECTIONS

WET HANDS THOROUGHLY AND RUB TOGETHER UNTIL DRY

OTHER INFORMATION

STORE AT A TEMPERATURE BELOW 110°F (43°C)

INACTIVE INGREDIENTS

WATER (AQUA), PROPYLENE GLYCOL, CARBOMER, GLYCERIN, FRAGRANCE (PARFUM), ISOPROPYL MYRISTATE, TOCOPHERYL ACETATE, AMINOMETHYL PROPANOL, MANNITOL, CELLULOSE, HYDROXYPROPYL METHYLCELLULOSE, CHROMIUM HYDROXIDE GREEN (CI 77289), YELLOW 5 (CI 19140)